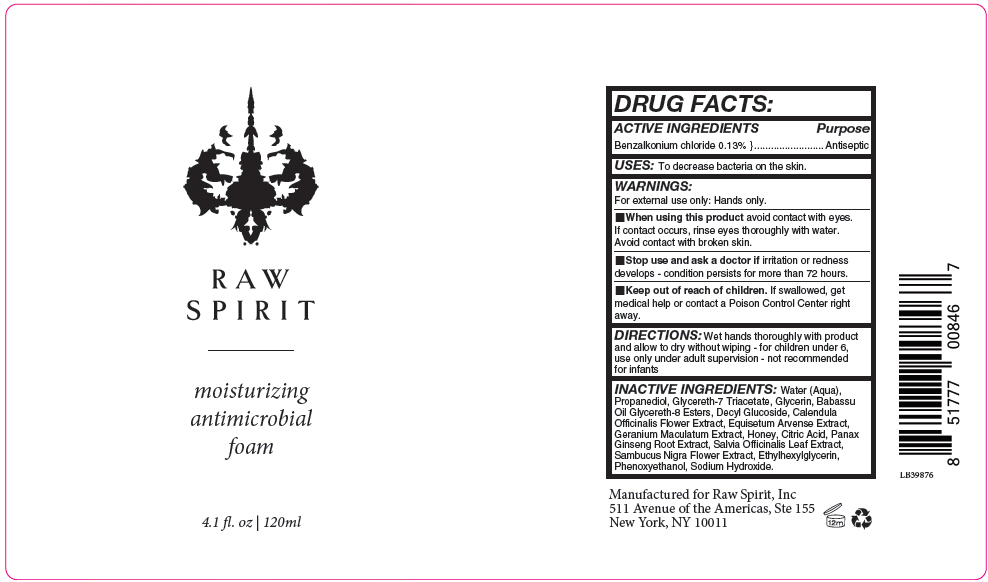 DRUG LABEL: Raw Spirit - Moisturizing Hand Sanitizer Foam
NDC: 66163-1901 | Form: LIQUID
Manufacturer: Cosmetic Solutions LLC
Category: otc | Type: HUMAN OTC DRUG LABEL
Date: 20200716

ACTIVE INGREDIENTS: BENZALKONIUM CHLORIDE 1.3 mg/10 mL
INACTIVE INGREDIENTS: Water; Propanediol; Glycereth-7 Triacetate; Glycerin; Babassu Oil Glycereth-8 Esters; Decyl Glucoside; Calendula Officinalis Flower; Equisetum Arvense Branch; Geranium Maculatum Root; Honey; Citric Acid Monohydrate; Asian Ginseng; Sambucus Nigra Flower; Ethylhexylglycerin; Phenoxyethanol; Sodium Hydroxide

Raw Spirit - Moisturizing Hand Sanitizer Foam

DRUG FACTS:

ACTIVE INGREDIENTS

Benzalkonium chloride 0.13%

Purpose

Antiseptic

USES

To decrease bacteria on the skin.

WARNINGS

For external use only: Hands only.

- When using this product avoid contact with eyes. If contact occurs, rinse eyes thoroughly with water. Avoid contact with broken skin.

- Stop use and ask a doctor if irritation or redness develops - condition persists for more than 72 hours.

- Keep out of reach of children. If swallowed, get medical help or contact a Poison Control Center right away.

DIRECTIONS

Wet hands thoroughly with product and allow to dry without wiping - for children under 6, use only under adult supervision - not recommended for infants

INACTIVE INGREDIENTS

Water (Aqua), Propanediol, Glycereth-7 Triacetate, Glycerin, Babassu Oil Glycereth-8 Esters, Decyl Glucoside, Calendula Officinalis Flower Extract, Equisetum Arvense Extract, Geranium Maculatum Extract, Honey, Citric Acid, Panax Ginseng Root Extract, Salvia Officinalis Leaf Extract, Sambucus Nigra Flower Extract, Ethylhexylglycerin, Phenoxyethanol, Sodium Hydroxide.

PRINCIPAL DISPLAY PANEL - 120 ml Bottle Label

RAW
SPIRIT

moisturizing
antimicrobial
foam

4.1 fl. oz | 120ml